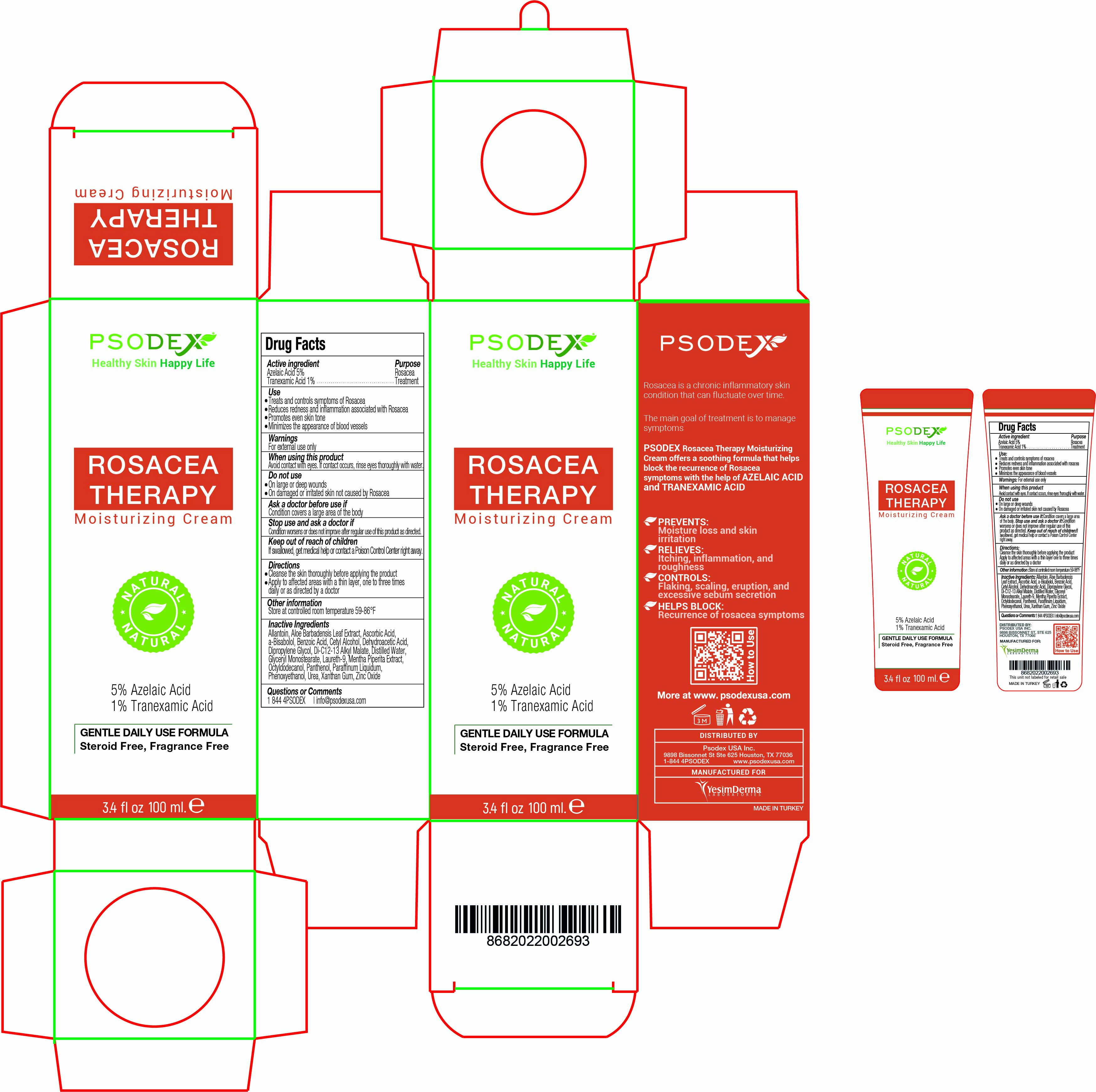 DRUG LABEL: Rosacea Therapy
NDC: 73503-009 | Form: CREAM
Manufacturer: PSODEX USA INC
Category: otc | Type: HUMAN OTC DRUG LABEL
Date: 20231229

ACTIVE INGREDIENTS: TRANEXAMIC ACID 1 g/100 mL; AZELAIC ACID 5 g/100 mL
INACTIVE INGREDIENTS: ALLANTOIN 2 g/100 mL; DEHYDROACETIC ACID 0.25 g/100 mL; MENTHA PIPERITA LEAF 5 g/100 mL; MINERAL OIL 5 g/100 mL; POLIDOCANOL 3 g/100 mL; PHENOXYETHANOL 0.5 g/100 mL; OCTYLDODECANOL 2 g/100 mL; ALOE VERA LEAF 5 g/100 mL; DIPROPYLENE GLYCOL 0.2 g/100 mL; ASCORBIC ACID 1 g/100 mL; WATER 43.5 mL/100 mL; UREA 5 g/100 mL; PANTHENOL 1 g/100 mL; LEVOMENOL 2 g/100 mL; GLYCERYL MONOSTEARATE 2 g/100 mL; XANTHAN GUM 0.3 g/100 mL; CETYL ALCOHOL 5 g/100 mL; DI-C12-13 ALKYL MALATE 2 g/100 mL; ZINC OXIDE 9 g/100 mL; BENZOIC ACID 0.25 g/100 mL

Rosacea Therapy Moisturizing Cream

Rosacea Therapy Moisturizing Cream

Rosacea is a chronic inflammatory skin condition that can fluctuate over time.

The main goal of treatment is to manage symptoms

PSODEX Rosacea Therapy Moisturizing Cream offers a soothing formula that helps block the recurrence of Rosacea symptoms with the help of AZELAIC ACID and TRANEXAMIC ACID

PREVENTS:
Moisture loss and skin irritation

RELIEVES:
Itching, inflammation, and roughness

CONTROLS:
Flaking, scaling, eruption, and excessive sebum secretion

HELPS BLOCK:
Recurrence of rosacea symptoms

Rosacea Therapy Moisturizing Cream Active ingredient:

Active ingredient:

Azelaic Acid 5%
Tranexamic Acid 1%

Purpose:

Rosacea Treatment

Rosacea Therapy Moisturizing Cream

Active ingredient:
Azelaic Acid 5%
Tranexamic Acid 1%

Rosacea Therapy Moisturizing Cream

Purpose:
Rosacea Treatment

Rosacea Therapy Moisturizing Cream

Inactive Ingredients:

Allantoin, Aloe Barbadensis Leaf Extract, Ascorbic Acid,
a-Bisabolol, Benzoic Acid, Cetyl Alcohol, Dehydroacetic Acid,
Dipropylene Glycol, Di-C12-13 Alkyl Malate, Distilled Water,
Glyceryl Monostearate, Laureth-9, Mentha Piperita Extract,
Octyldodecanol, Panthenol, Paraffinum Liquidum,
Phenoxyethanol, Urea, Xanthan Gum, Zinc Oxide

Rosacea Therapy Moisturizing Cream

Directions:

Cleanse the skin thoroughly before applying the product
Apply to affected areas with a thin layer, one to three times
daily or as directed by a doctor

Rosacea Therapy Moisturizing Cream

DISTRIBUTED BY: Psodex USA Inc.

9898 Bissonnet St Ste 625 Houston, TX 77036

1-844 4PSODEX www.psodexusa.com

MANUFACTURED FOR

Yesim Derma Laboratories

Rosacea Therapy Moisturizing Cream

Ask a doctor before use if : Condition covers a large area of the body

Rosacea Therapy Moisturizing Cream

Do not use:

On large or deep wounds
On damaged or irritated skin not caused by Rosacea

Rosacea Therapy Moisturizing Cream

Keep out of reach of children: If swallowed, get medical help or contact a Poison Control Center right away.

Questions or Comments:

1 844 4PSODEX | info@psodexusa.com

Stop use and ask a doctor if

Condition worsens or does not improve after regular use of this product as directed.

When using this product

Avoid contact with eyes. If contact occurs, rinse eyes thoroughly with water.

Other information

Store at controlled room temperature 59-86°F

Warnings

For external use only

Use

Treats and controls symptoms of Rosacea
Reduces redness and inflammation associated with Rosacea
Promotes even skin tone
Minimizes the appearance of blood vessels